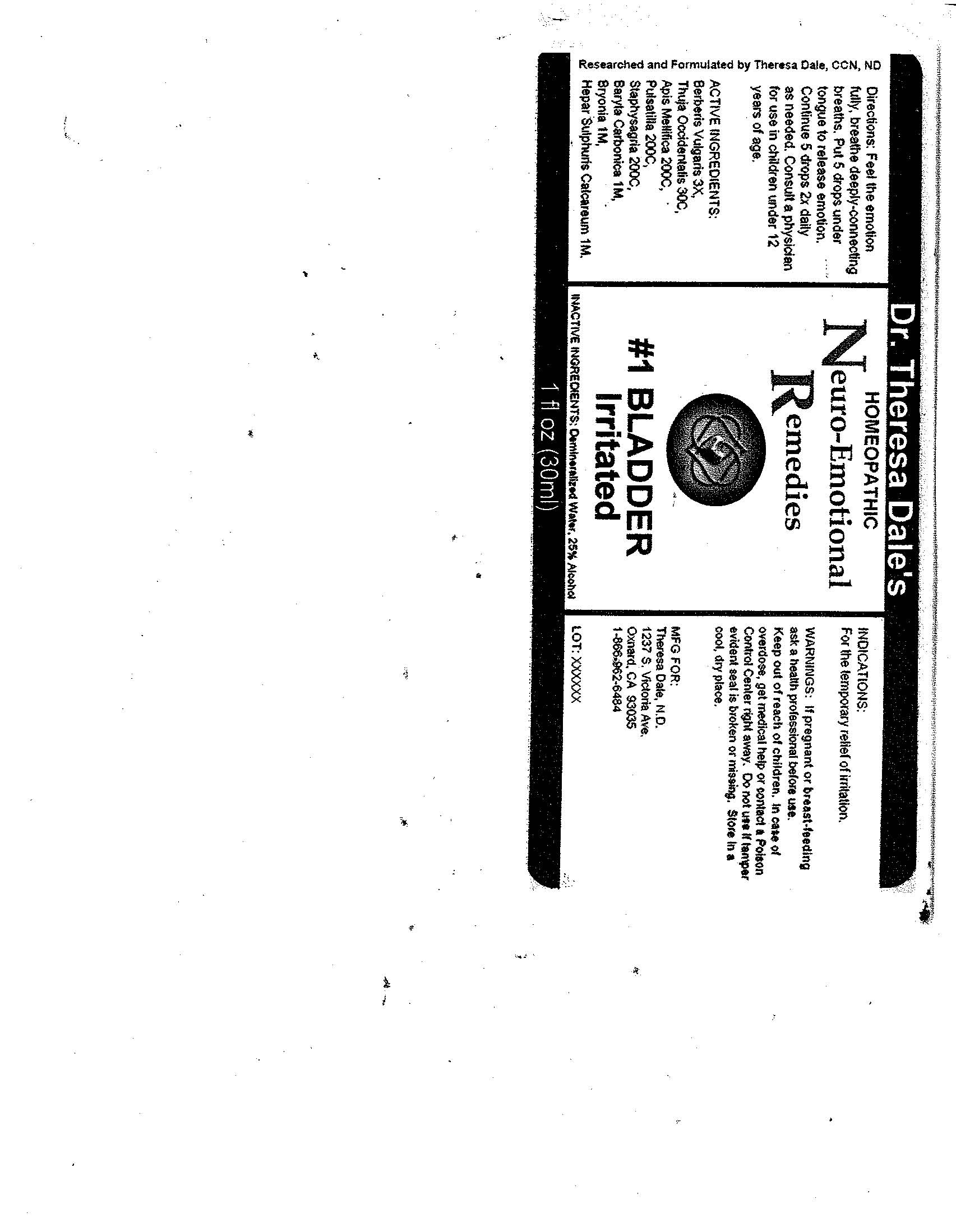 DRUG LABEL: 1 Bladder
NDC: 57520-0220 | Form: LIQUID
Manufacturer: Apotheca, Company
Category: homeopathic | Type: HUMAN OTC DRUG LABEL
Date: 20100707

ACTIVE INGREDIENTS: BERBERIS VULGARIS ROOT BARK 3 [hp_X]/1 mL; THUJA OCCIDENTALIS LEAFY TWIG 30 [hp_C]/1 mL; APIS MELLIFERA 200 [hp_C]/1 mL; PULSATILLA VULGARIS 200 [hp_C]/1 mL; DELPHINIUM STAPHISAGRIA SEED 200 [hp_C]/1 mL; BARIUM CARBONATE 1 [hp_M]/1 mL; BRYONIA ALBA ROOT 1 [hp_M]/1 mL; CALCIUM SULFIDE 1 [hp_M]/1 mL
INACTIVE INGREDIENTS: WATER; ALCOHOL

#1 Bladder

ACTIVE INGREDIENT

ACTIVE INGREDIENTS: Berberis vulgaris 3X, Thuja occidentalis 30C, Apis mellifica 200C, Pulsatilla 200C, Staphysagria 200C, Baryta carbonica 1M, Bryonia 1M, Hepar sulphuris calcareum 1M.

PURPOSE

INDICATIONS: For the temporary relief of irritation.

WARNINGS

WARNINGS: If pregnant or breast-feeding, ask a health professional before use.

Keep out of reach of children. In case of overdose, get medical help or contact a Poison Control Center right away.

Do not use if tamper evident seal is broken or missing. Store in a cool, dry place.

DOSAGE AND ADMINISTRATION

DIRECTIONS: Feel the emotion fully, breathe deeply-connecting breaths. Put 5 drops under tongue to release emotion. Continue 5 drops 2 times daily as needed. Consult a physician for use in children under 12 years of age.

INACTIVE INGREDIENTS: Demineralized water, 25% Alcohol

QUESTIONS

MFG. FOR:

Theresa Dale, N.D.

1237 S. Victoria Ave.

Oxnard, CA 93035

1-866-962-6484

PACKAGE LABEL

Dr. Theresa Dale's

HOMEOPATHIC

Neuro-Emotional Remedies

#1 BLADDER

Irritated

1 fl oz (30 ml)